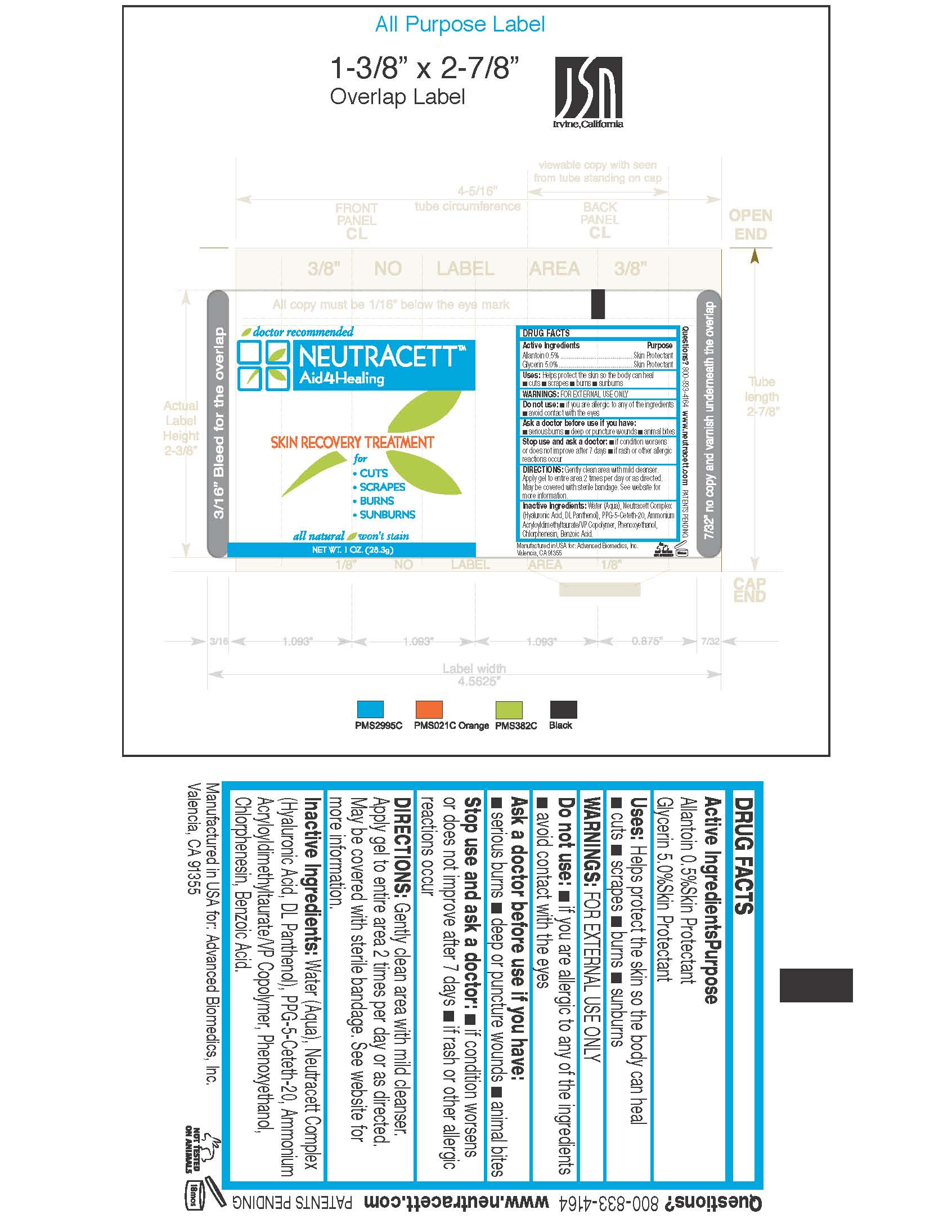 DRUG LABEL: NEUTRACETT
NDC: 51435-003 | Form: GEL
Manufacturer: ADVANCED BIOMEDICS INC
Category: otc | Type: HUMAN OTC DRUG LABEL
Date: 20101109

ACTIVE INGREDIENTS: ALLANTOIN 0.5 mg/0.1 g; GLYCERIN 50 mg/1 g
INACTIVE INGREDIENTS: WATER; HYALURONIC ACID; PANTHENOL; PPG-5-CETETH-20; PHENOXYETHANOL; CHLORPHENESIN; BENZOIC ACID

TUBE LABEL

INACTIVE INGREDIENT

Inactive Ingredients: Water (Aqua), Neutracett Complex (Hyaluronic Acid, DL Panthenol), PPG-5-Ceteth-20, Ammonium Acryloyldimethyltaurate/VP Copolymer, Phenoxyethanol, Chlorphenesin, Benzoic Acid.

Active ingredients

Allantoin 0.5%

Glycerin 5.0%

Ask a doctor before use if you have: *serious burns * deep or puncture wounds * animal bites

Questions? 800-833-4164

www.neutracett.com Patents Pending

Do not use: *if you are allergic to any of the ingredients *avoid contact with the eyes

Stop use and ask a doctor: * if condition worsens or does not improve after 7 days * if rash or other allergic reactions occur

Purpose: Skin Protectant

Warnings: For external use only.

DOSAGE AND ADMINISTRATION

Directions: Gently clean area with mild cleanser. Apply gel to entire area 2 times per day or as directed. May be covered with sterile bandage. See website for more information.

PACKAGE LABEL

Neutracett

Aid 4-Healing

Skin Recovery Treatment

For cuts, scrapes, burns and sunburns

All natural / won’t stain

Keep out of reach of children.

INDICATIONS AND USAGE

Uses: Helps protect the skin so your body can heal cuts, scrapes, burns and sunburns.